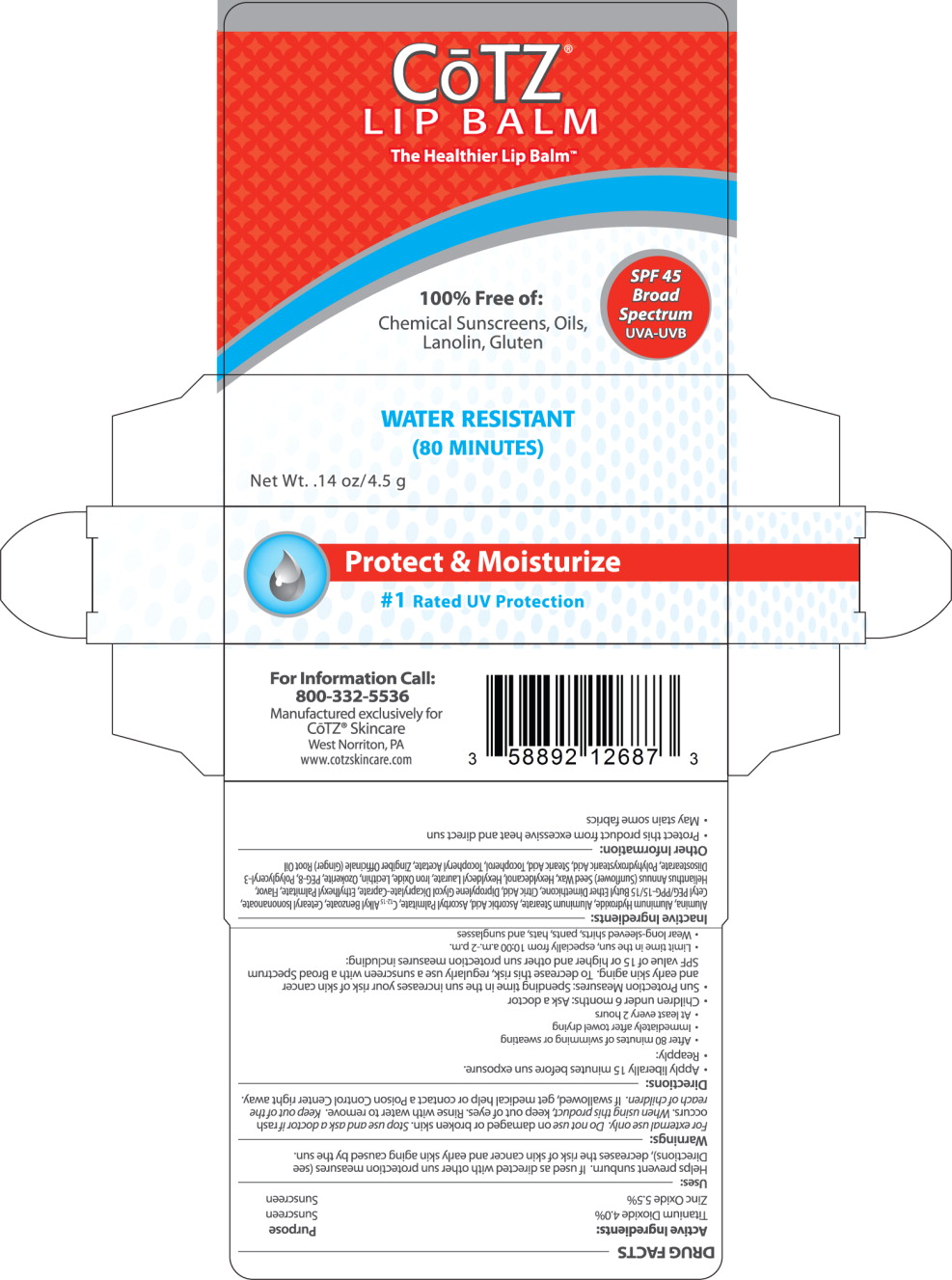 DRUG LABEL: Cotz Lip Balm 
NDC: 58892-126 | Form: LIPSTICK
Manufacturer: Fallien Cosmeceuticals, LTD.
Category: otc | Type: HUMAN OTC DRUG LABEL
Date: 20121228

ACTIVE INGREDIENTS: Titanium Dioxide 40 mg/1 g; Zinc Oxide 55 mg/1 g
INACTIVE INGREDIENTS: Aluminum Oxide; Aluminum Hydroxide; Aluminum Stearate; Ascorbic Acid; Ascorbyl Palmitate; C12-15 Alkyl Benzoate; Ceresin; Cetearyl Isononanoate; Anhydrous Citric Acid; Propylene Glycol Dicaprylate/Dicaprate; Ethylhexyl Palmitate; Kiwi Fruit; Lime (Citrus); Sunflower Oil; Hexyldecanol; Hexyldecyl Laurate; Ferric Oxide Red; Lecithin, Soybean; Polyethylene Glycol 400; Stearic Acid; .Alpha.-Tocopherol; .ALPHA.-Tocopherol Acetate, D-; Ginger Oil

DRUG FACTS

Active Ingredients:

Titanium Dioxide 4.0%

Zinc Oxide 5.5%

Purpose

Sunscreen

Sunscreen

Uses:

Helps prevent sunburn. If used as directed with other sun protection measures (see Directions), decreases the risk of skin cancer and early skin aging caused by the sun.

Warnings:

For external use only.

Do not use on damaged or broken skin.

Stop use and ask a doctor if rash occurs.

When using this product, keep out of eyes. Rinse with water to remove.

KEEP OUT OF REACH OF CHILDREN

Keep out of the reach of children, if swallowed, get medical help or contact a Poison Control Center right away.

Directions:

- Apply liberally 15 minutes before sun exposure.
- Reapply:
  - After 80 minutes of swimming or sweating
  - Immediately after towel drying
  - At least every 2 hours
- Children under 6 months: Ask a doctor
- Sun Protection Measures: Spending time in the sun increases your risk of skin cancer and early skin aging. To decrease this risk, regularly use a sunscreen with a Broad Spectrum SPF value of 15 or higher and other sun protection measures including:
  - Limit time in the sun, especially from 10:00 a.m.-2 p.m.
  - Wear long-sleeved shirts, pants, hats, and sunglasses

Inactive Ingredients:

Alumina, Aluminum Hydroxide, Aluminum Stearate, Ascorbic Add, Ascorbyl Palmitate, C 12-15 Alkyl Benzoate, Cetearyl Isononanoate, Cetyl PEG/PPG-15/15 Butyl Ether Dimethicone, Citric Add, Dipropylene Glycol Dicaprylate-Caprate, Ethylhexyl Palmitate, Flavor, Helianthus Annuus (Sunflower) Seed Wax, Hexyldecanol, Hexyldecyl Laurate, Iron Oxide, Lecithin, Ozokerite, PEG-8, Polyglyceryl-3 Diisostearate, Polyhydroxystearic Acid, Stearic Acid, Tocopherol, Tocopheryl Acetate, Zingiber Officinale (Ginger) Root Oil

Other Information:

- Protect this product from excessive heat and direct sun
- May stain some fabrics

Principal Display Panel – 4.5 g Carton Label

CoTZ®

LIP BALM

The Healthier Lip Balm TM

100% Free of:

Chemical Sunscreens, Oils,

Lanolin, Gluten

SPF45

Broad

Spectrum

UVA-UVB

WATER RESISTANT

(80 MINUTES)

Net Wt. .14 oz/4.5 g